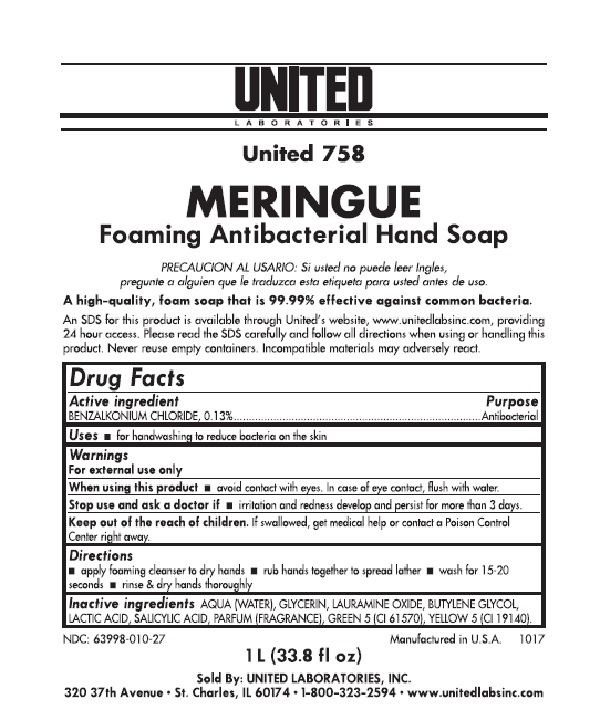 DRUG LABEL: MERINGUE
NDC: 63998-010 | Form: SOLUTION
Manufacturer: United Laboratories, Inc.
Category: otc | Type: HUMAN OTC DRUG LABEL
Date: 20180111

ACTIVE INGREDIENTS: BENZALKONIUM CHLORIDE 0.13 g/100 mL
INACTIVE INGREDIENTS: WATER; GLYCERIN; LAURAMINE OXIDE; BUTYLENE GLYCOL; LACTIC ACID; SALICYLIC ACID; D&C GREEN NO. 5; FD&C YELLOW NO. 5

Drug Facts

Active ingredient

BENZALKONIUM CHLORIDE, 0.13%

Purpose

Antibacterial

Uses

for handwashing to reduce bacteria on the skin

Warnings

When using this product

avoid contact with eyes. In case of eye contact, flush with water.

Stop use and ask a doctor if

irritation and redness develop and persist for more than 3 days.

Keep out of reach of children.

If swallowed, get medical help or contact a Poison Control Center right away.

Directions

apply foaming cleanser to dry hands
rub hands together to spread lather
wash for 15-20 seconds
rinse & dry hands thoroughly

Inactive ingredients

AQUA (WATER), GLYCERIN, LAURAMINE OXIDE, BUTYLENE GLYCOL, LACTIC ACID, SALICYLIC ACID, PARFUM (FRAGRANCE), GREEN 5 (CI 61570), YELLOW 5 (CI 19140).

PACKAGE LABEL

UNITED LABORATORIES

United 758
MERINGUE
Foaming Antibacterial Hand Soap
PRECAUCION AL USARIO: Si usted no pede leer Ingles, pregunte a alguien que le traduzca esta etigueta para usted antes de uso.
A high-quality, foam soap that is 99.99% effective against common bacteria.
An SDS for this product is available through United’s website, www.unitedlabsinc.com, providing 24 hour access. Please read the SDS carefully and follow all directions when using or handling this product. Never reuse empty containers. Incompatible materials may adversely react.
NDC 63998-010-27
Manufactured in U.S.A.
1017
1 L (33.8 fl oz)

Sold By: UNITED LABORATORIES, INC.

320 37th Avenue ● St. Charles, IL 60174 ● 1-800-323-2594 ● www.unitedlabsinc.com